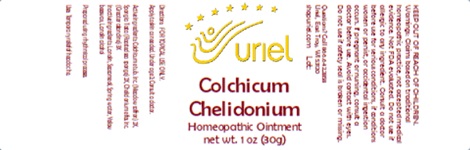 DRUG LABEL: Colchicum Chelidonium
NDC: 48951-3271 | Form: OINTMENT
Manufacturer: Uriel Pharmacy, Inc.
Category: homeopathic | Type: HUMAN OTC DRUG LABEL
Date: 20251204

ACTIVE INGREDIENTS: CHELIDONIUM MAJUS FLOWERING TOP 3 [hp_X]/1 g; COLCHICUM AUTUMNALE WHOLE 2 [hp_X]/1 g; SPONGIA OFFICINALIS SKELETON, ROASTED 2 [hp_X]/1 g
INACTIVE INGREDIENTS: SUNFLOWER OIL; LANOLIN ALCOHOL; BEESWAX; LANOLIN; WATER

Colchicum Chelidonium

INDICATIONS AND USAGE

Directions: FOR TOPICAL USE ONLY.

DOSAGE AND ADMINISTRATION

Apply to skin as needed. Under age 2: Consult a doctor.

Active Ingredient: Colchicum e tub. Inc.(Meadow saffron) 2X, Spongia tosta (Roasted sea sponge) 2X, Chelidonium e flos. Inc. (Greater celandine) 3X

INACTIVE INGREDIENT

Inactive Ingredients: Lanolin, Sunflower seed oil, Water, Yellow beeswax, Lanolin alcohol

Prepared using rhythmical processes.

PURPOSE

Use: Temporary relief of headache.

KEEP OUT OF REACH OF CHILDREN.

WARNINGS

Warnings: Claims based on traditional homeopathic practice, not accepted medical evidence. Not FDA evaluated. Do not use if allergic to any ingredient. Consult a doctor before use for serious conditions, if conditions worsen or persist, or accidental ingestion occurs. If pregnant or nursing, consult a doctor before use. Avoid contact with eyes. Do not use if safety seal is broken or missing.

Questions? Call 866.642.2858
Made with care by Uriel, East Troy, WI 53120
shopuriel.com Lot: